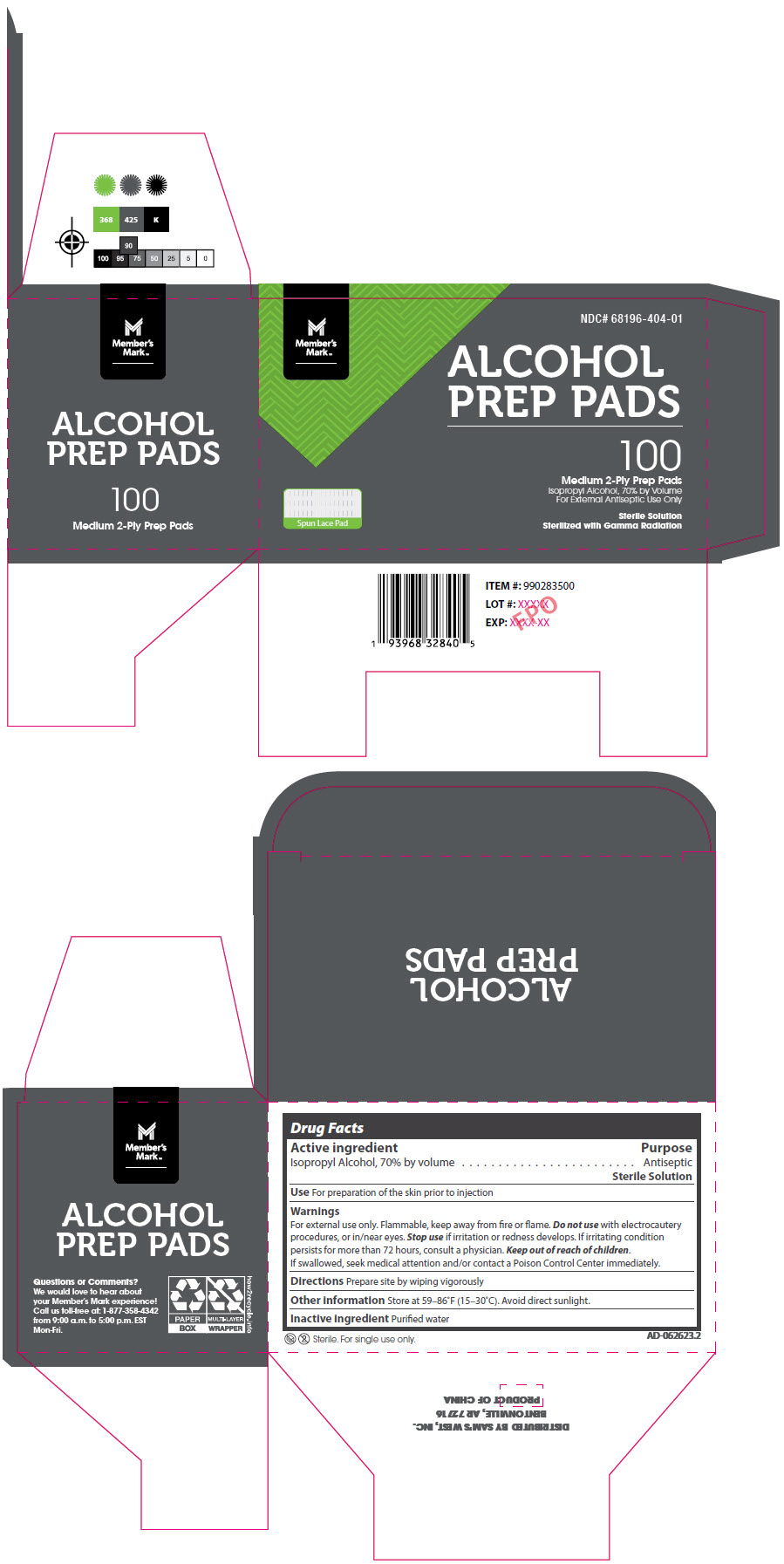 DRUG LABEL: Members Mark Alcohol Prep Pads, Sterile
NDC: 68196-404 | Form: SWAB
Manufacturer: Sam's Club West Inc.
Category: otc | Type: HUMAN OTC DRUG LABEL
Date: 20250122

ACTIVE INGREDIENTS: Isopropyl Alcohol 70 mL/100 mL
INACTIVE INGREDIENTS: Water

Member's Mark™ Alcohol Prep Pads, Sterile

Drug Facts

Active ingredient

Isopropyl Alcohol, 70% by volume

Purpose

Antiseptic
Sterile Solution

Use

For preparation of the skin prior to injection

Warnings

For external use only. Flammable, keep away from fire or flame.

Do not use with electrocautery procedures, or in/near eyes.

Stop use if irritation or redness develops. If irritating condition persists for more than 72 hours, consult a physician.

Keep out of reach of children.

If swallowed, seek medical attention and/or contact a Poison Control Center immediately.

Directions

Prepare site by wiping vigorously

Other information

Store at 59–86°F (15–30°C). Avoid direct sunlight.

Inactive ingredient

Purified water

Questions or Comments?

We would love to hear about your Member's Mark experience! Call us toll-free at: 1-877-358-4342 from 9:00 a.m. to 5:00 p.m. EST Mon-Fri.

DISTRIBUTED BY SAM'S WEST, INC.
BENTONVILLE, AR 72716

PRINCIPAL DISPLAY PANEL - 100 Pad Pouch Box

Member's
Mark™

NDC# 68196-404-01

ALCOHOL
PREP PADS

100
Medium 2-Ply Prep Pads
Isopropyl Alcohol, 70% by Volume
For External Antiseptic Use Only

Sterile Solution
Sterilized with Gamma Radiation

Spun Lace Pad